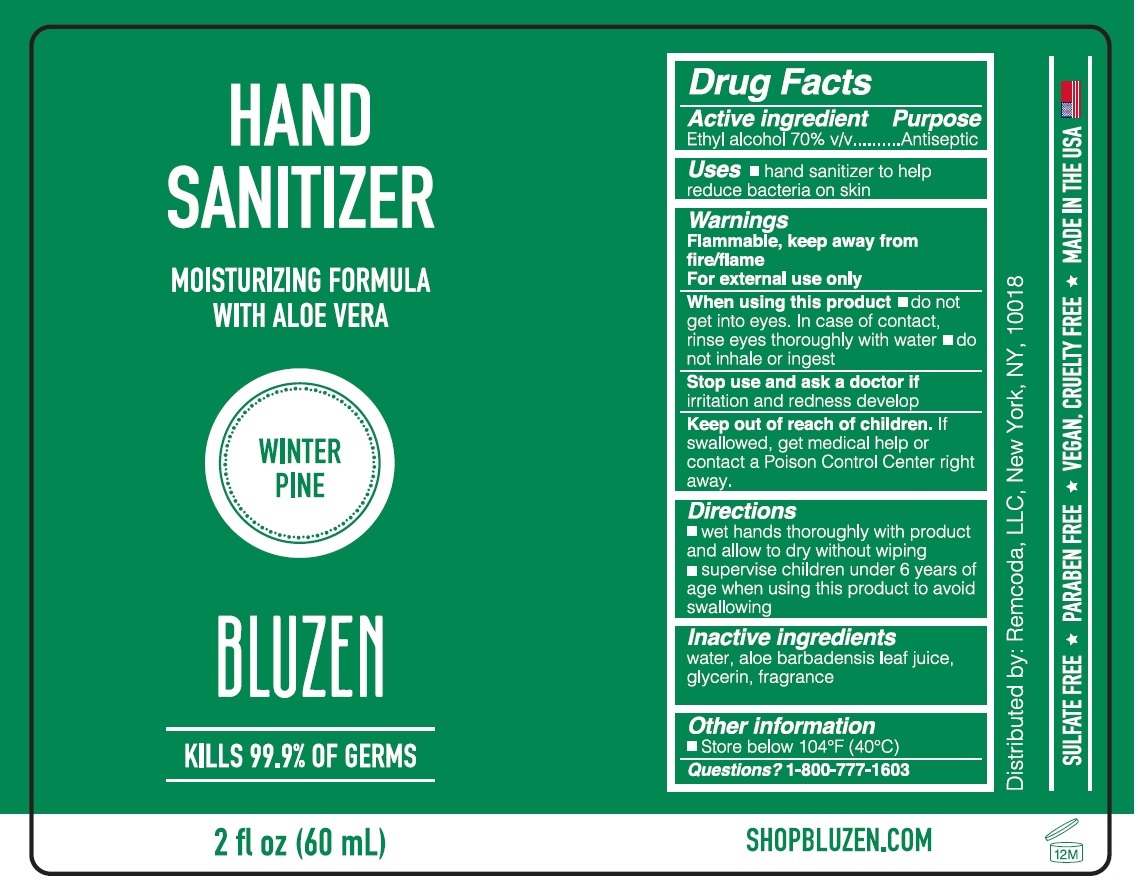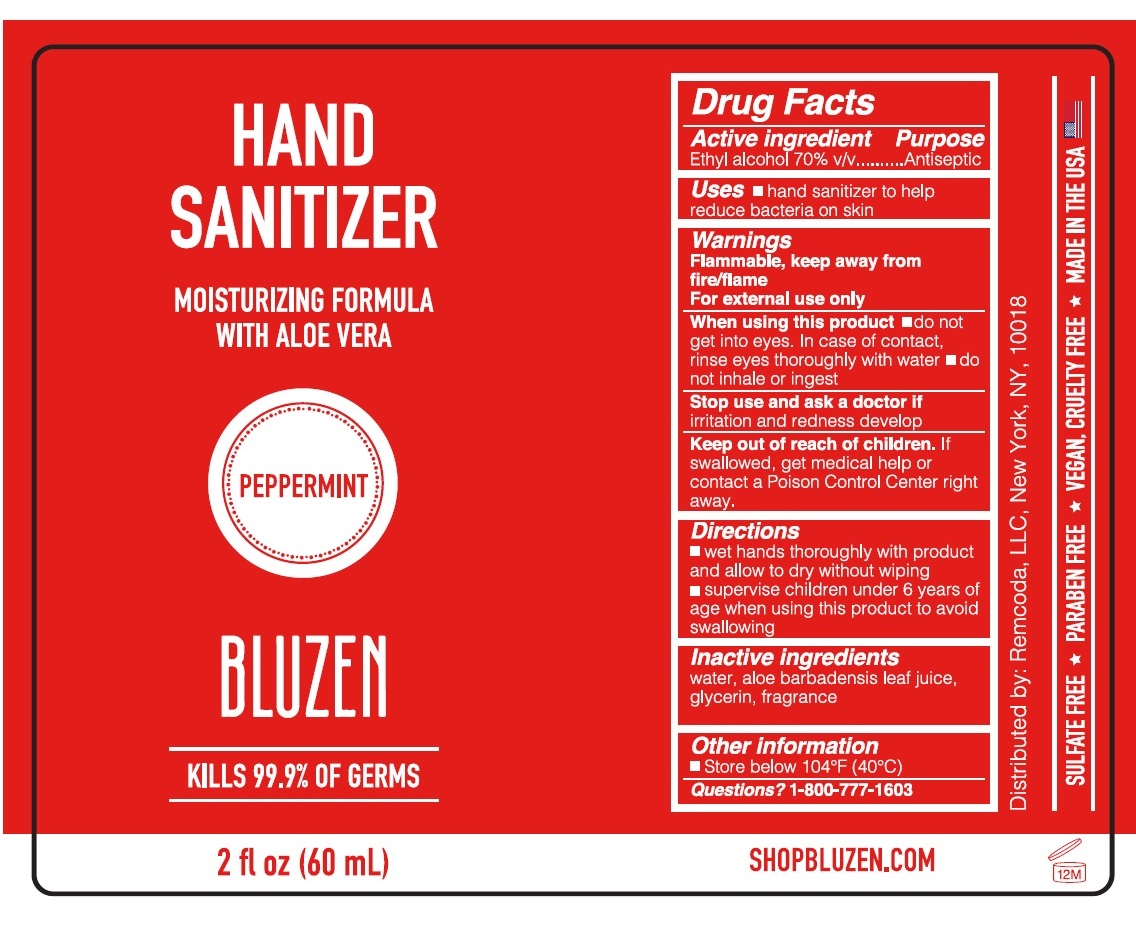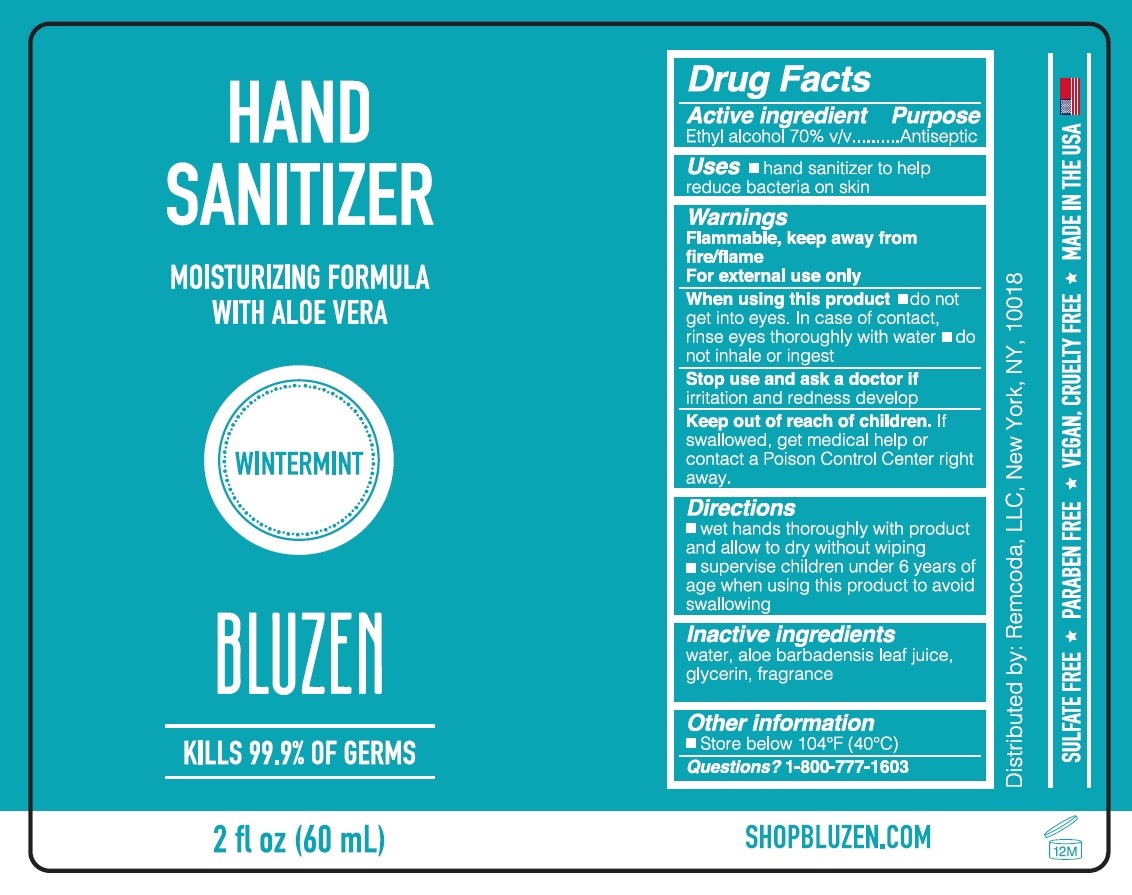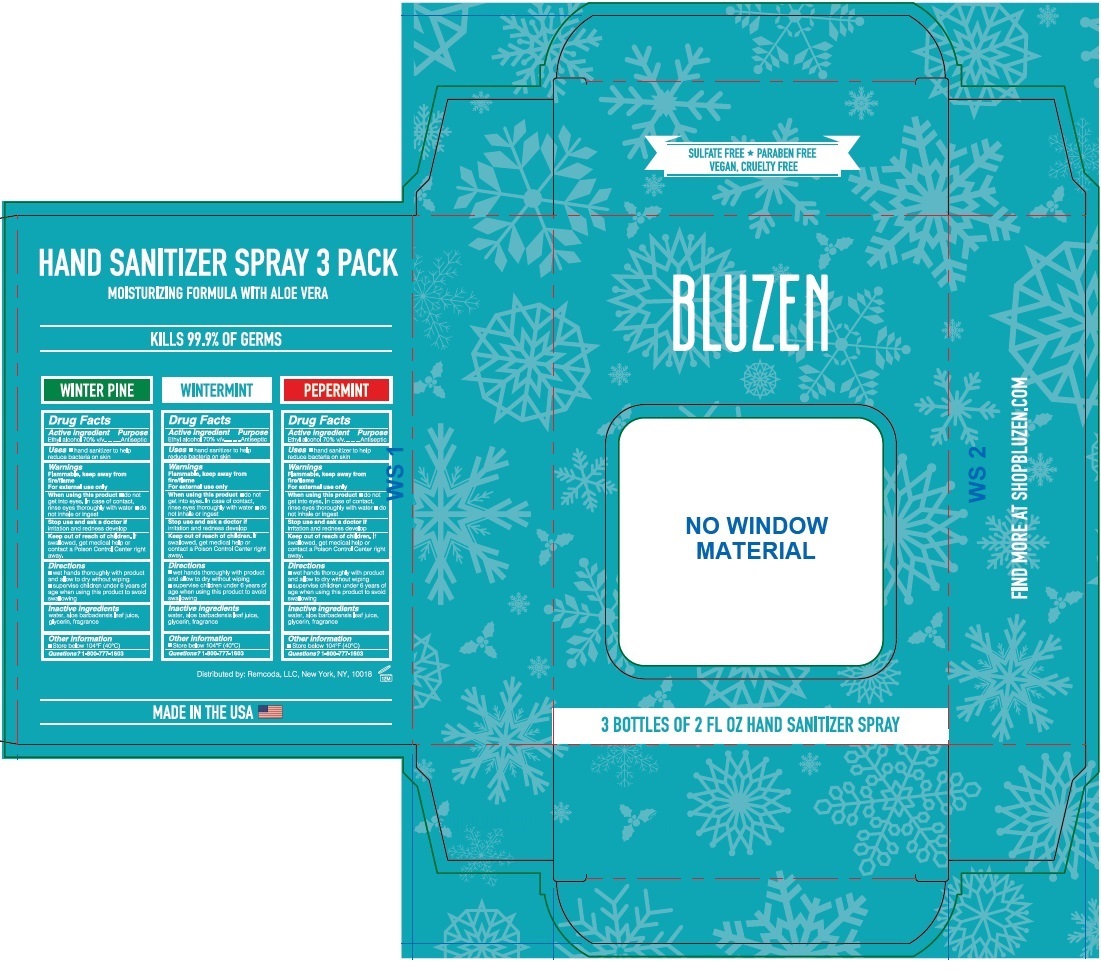 DRUG LABEL: BluZen - Winter Pine, Wintermint, Peppermint - Kit
NDC: 79200-705 | Form: KIT | Route: TOPICAL
Manufacturer: Remcoda, Llc
Category: otc | Type: HUMAN OTC DRUG LABEL
Date: 20200911

ACTIVE INGREDIENTS: ALCOHOL 70 mL/100 mL; ALCOHOL 70 mL/100 mL; ALCOHOL 70 mL/100 mL
INACTIVE INGREDIENTS: WATER; ALOE VERA LEAF; GLYCERIN; WATER; ALOE VERA LEAF; GLYCERIN; WATER; ALOE VERA LEAF; GLYCERIN

BLUZEN HAND SANITIZER KIT

BLUZEN HAND SANITIZER WINTER PINE

Drug Facts

Active ingredient

Ethyl alcohol 70% v/v

Purpose

Antiseptic

INDICATIONS AND USAGE

Uses ■ hand sanitizer to help reduce bacteria on skin

Warnings

Flammable, keep away from fire/flame

For external use only

When using this product ■ do not get into eyes. In case of contact, rinse eyes thoroughly with water

■ do not inhale or ingest

Stop use and ask a doctor if irritation and redness develop

Keep out of reach of children. If swallowed, get medical help or contact a Poison Control Center right away.

Directions

■ wet hands thoroughly with product and allow to dry without wiping

■ supervise children under 6 years of age when using this product to avoid swallowing

Other information

■ Store below 104°F (40°C)

Inactive ingredients

water, aloe barbadensis leaf juice, glycerin, fragrance

Questions? 1-800-777-1603

MOISTURIZING FORMULA WITH ALOE VERA

KILLS 99.9% OF GERMS

SULFATE FREE PARABEN FREE VEGAN, CRUELTY FREE

MADE IN THE USA

Distributed by: Remcoda, LLC, New York, NY, 10018

SHOPBLUZEN.COM

BLUZEN HAND SANITIZER PEPPERMINT

Drug Facts

Active ingredient

Ethyl alcohol 70% v/v

Purpose

Antiseptic

INDICATIONS AND USAGE

Uses ■ hand sanitizer to help reduce bacteria on skin

Warnings

Flammable, keep away from fire/flame

For external use only

When using this product ■ do not get into eyes. In case of contact, rinse eyes thoroughly with water

■ do not inhale or ingest

Stop use and ask a doctor if irritation and redness develop

Keep out of reach of children. If swallowed, get medical help or contact a Poison Control Center right away.

Directions

■ wet hands thoroughly with product and allow to dry without wiping

■ supervise children under 6 years of age when using this product to avoid swallowing

Other information

■ Store below 104°F (40°C)

Inactive ingredients

water, aloe barbadensis leaf juice, glycerin, fragrance

Questions? 1-800-777-1603

MOISTURIZING FORMULA WITH ALOE VERA

KILLS 99.9% OF GERMS

SULFATE FREE PARABEN FREE VEGAN, CRUELTY FREE

MADE IN THE USA

Distributed by: Remcoda, LLC, New York, NY, 10018

SHOPBLUZEN.COM

BLUZEN HAND SANITIZER WINTERMINT

Drug Facts

Active ingredient

Ethyl alcohol 70% v/v

Purpose

Antiseptic

INDICATIONS AND USAGE

Uses ■ hand sanitizer to help reduce bacteria on skin

Warnings

Flammable, keep away from fire/flame

For external use only

When using this product ■ do not get into eyes. In case of contact, rinse eyes thoroughly with water

■ do not inhale or ingest

Stop use and ask a doctor if irritation and redness develop

Keep out of reach of children. If swallowed, get medical help or contact a Poison Control Center right away.

Directions

■ wet hands thoroughly with product and allow to dry without wiping

■ supervise children under 6 years of age when using this product to avoid swallowing

Other information

■ Store below 104°F (40°C)

Inactive ingredients

water, aloe barbadensis leaf juice, glycerin, fragrance

Questions? 1-800-777-1603

MOISTURIZING FORMULA WITH ALOE VERA

KILLS 99.9% OF GERMS

SULFATE FREE PARABEN FREE VEGAN, CRUELTY FREE

MADE IN THE USA

Distributed by: Remcoda, LLC, New York, NY, 10018

SHOPBLUZEN.COM